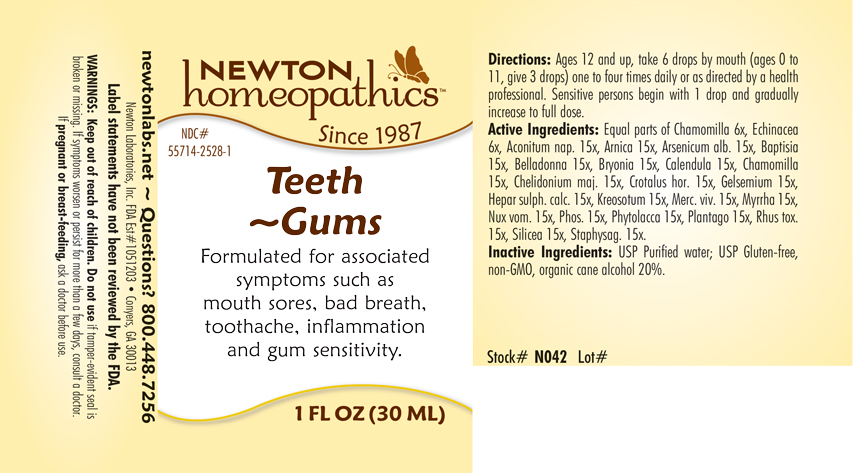 DRUG LABEL: Teeth-Gums
NDC: 55714-2528 | Form: LIQUID
Manufacturer: Newton Laboratories, Inc.
Category: homeopathic | Type: HUMAN OTC DRUG LABEL
Date: 20250210

ACTIVE INGREDIENTS: DELPHINIUM STAPHISAGRIA SEED 15 [hp_X]/1 mL; ECHINACEA, UNSPECIFIED 6 [hp_X]/1 mL; ARSENIC TRIOXIDE 15 [hp_X]/1 mL; BAPTISIA TINCTORIA ROOT 15 [hp_X]/1 mL; ATROPA BELLADONNA 15 [hp_X]/1 mL; BRYONIA ALBA ROOT 15 [hp_X]/1 mL; CALENDULA OFFICINALIS FLOWERING TOP 15 [hp_X]/1 mL; MATRICARIA CHAMOMILLA 15 [hp_X]/1 mL; CHELIDONIUM MAJUS 15 [hp_X]/1 mL; CROTALUS HORRIDUS HORRIDUS VENOM 15 [hp_X]/1 mL; ACONITUM NAPELLUS 15 [hp_X]/1 mL; CALCIUM SULFIDE 15 [hp_X]/1 mL; WOOD CREOSOTE 15 [hp_X]/1 mL; MERCURY 15 [hp_X]/1 mL; MYRRH 15 [hp_X]/1 mL; STRYCHNOS NUX-VOMICA SEED 15 [hp_X]/1 mL; PHOSPHORUS 15 [hp_X]/1 mL; PHYTOLACCA AMERICANA ROOT 15 [hp_X]/1 mL; PLANTAGO MAJOR 15 [hp_X]/1 mL; TOXICODENDRON PUBESCENS LEAF 15 [hp_X]/1 mL; SILICON DIOXIDE 15 [hp_X]/1 mL; ARNICA MONTANA 15 [hp_X]/1 mL; GELSEMIUM SEMPERVIRENS ROOT 15 [hp_X]/1 mL
INACTIVE INGREDIENTS: ALCOHOL; WATER

Teeth 2528L

INDICATIONS & USAGE SECTION

Formulated for associated symptoms such as mouth sores, bad breath, toothache, inflammation and gum sensitivity.

OTC - ACTIVE INGREDIENT SECTION

Equal parts of Chamomilla 6x, Echinacea 6x, Aconitum napellus 15x, Arnica montana 15x, Arsenicum album 15x, Baptisia tinctoria 15x, Belladonna 15x, Bryonia 15x, Calendula officinalis 15x, Chamomilla 15x, Chelidonium majus 15x, Crotalus horridus 15x, Gelsemium sempervirens 15x, Hepar sulphuris calcareum 15x, Kreosotum 15x, Mercurius vivus 15x, Myrrha 15x, Nux vomica 15x, Phosphorus 15x, Phytolacca decandra 15x, Plantago major 15x, Rhus toxicodendron 15x, Silicea 15x, Staphysagria 15x.

OTC - PURPOSE SECTION

Formulated for associated symptoms such as mouth sores, bad breath, toothache, inflammation and gum sensitivity.

INACTIVE INGREDIENT SECTION

USP Purified Water; USP Gluten-free, non-GMO, organic cane alcohol 20%.

QUESTIONS SECTION

newtonlabs.net – Questions? 800.448.7256

Newton Laboratories, Inc. FDA Est # 1051203 - Conyers, GA 30013

WARNINGS SECTION

WARNINGS: Keep out of reach of children. Do not use if tamper-evident seal is broken or missing. If symptoms worsen or persist for more than a few days, consult a doctor. If pregnant or breast-feeding, ask a doctor before use.

OTC - PREGNANCY OR BREAST FEEDING SECTION

If pregnant or breast-feeding, ask a doctor before use.

OTC - KEEP OUT OF REACH OF CHILDREN SECTION

Keep out of reach of children.

DOSAGE & ADMINISTRATION SECTION

Directions: Ages 12 and up, take 6 drops by mouth (ages 0 to 11, give 3 drops) one to four times daily or as directed by a health professional. Sensitive person begin with 1 drop and gradually increase to full dose.